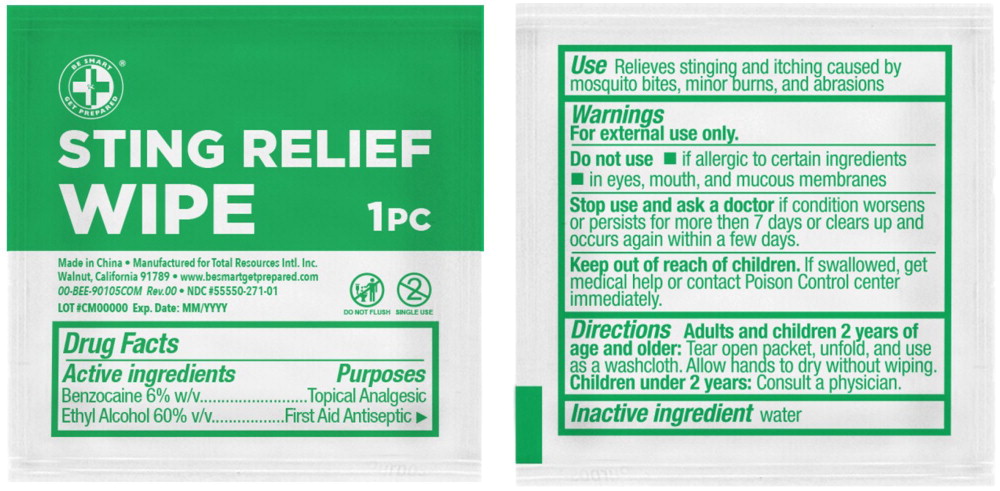 DRUG LABEL: Be Smart Get Prepared Sting Relief  Wipe
NDC: 55550-271 | Form: CLOTH
Manufacturer: Total Resources International, Inc
Category: otc | Type: HUMAN OTC DRUG LABEL
Date: 20251010

ACTIVE INGREDIENTS: BENZOCAINE 6 g/100 mL; ALCOHOL 60 mL/100 mL
INACTIVE INGREDIENTS: WATER

BE SMART GET PREPARED STING RELIEF WIPE

Active Ingredients

Benzocaine 6% w/v

Ethyl Alcohol 60% v/v

Purposes

Topical Analgesic

First Aid Antiseptic

USE

Relieves stinging and itching caused by mosquito bites, minor burns, and abrasions

WARNINGS

For external use only.

Do not use

- If allergic to certain ingredients
- In eyes, mouth, and mucous membranes

Stop use and ask the doctor if condition worsens or persists for more than 7 days or clears up and occurs again within a few days.

Keep out of reach of children. If swallowed, get medical help or contact Poison Control center immediately.

DIRECTIONS

Adults and children 2 years of age and older: tear open packet, unfold, and use as a washcloth. Allow hands to dry without wiping. Children under 2 years: Consult a physician

INACTIVE INGREDIENT

water

Principal Display Panel

BE SMART

GET PREPARED®

STING RELIEF WIPE 1 PC

Do Not Flush

Single Use

Made in China

Manufactured for Total Resources Intl. Inc.

Walnut, California 91789

www.besmartgetprepared.com • 00-BEE-90105COM Rev. 00

NDC 55550-271-01